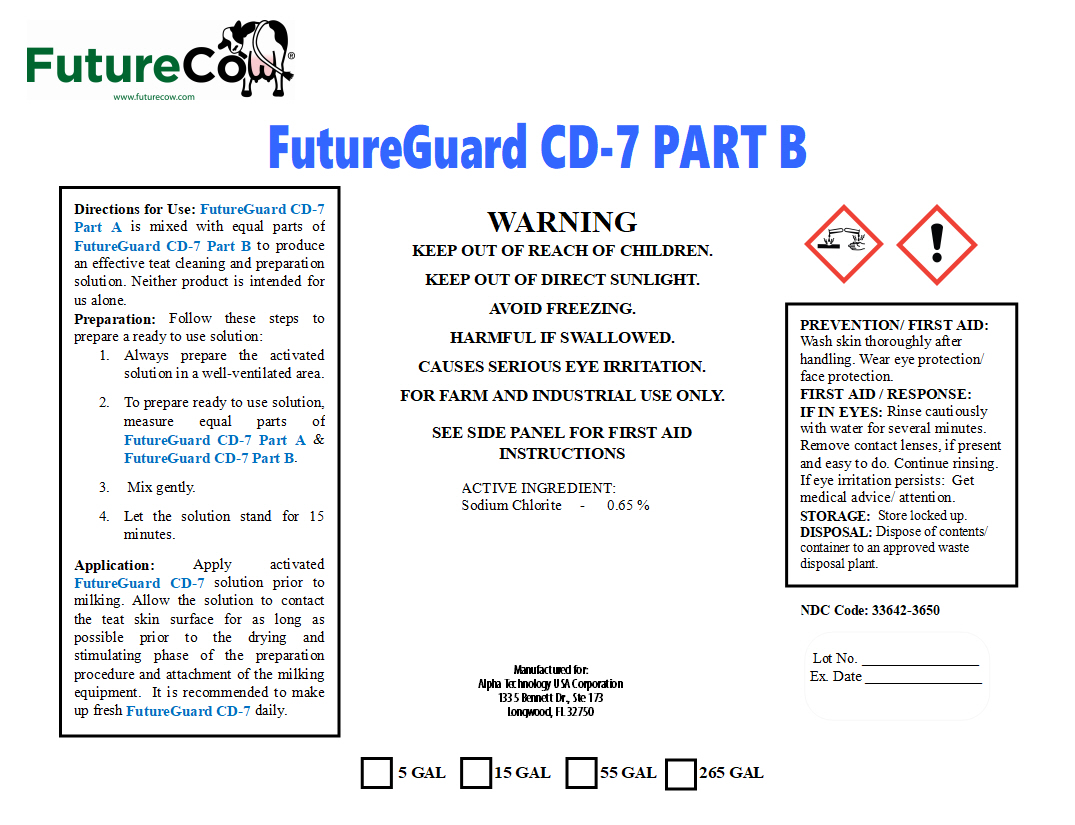 DRUG LABEL: FutureGuard CD-7 Part B
NDC: 33642-3650 | Form: SOLUTION
Manufacturer: Alpha Technology USA Corp.
Category: animal | Type: OTC ANIMAL DRUG LABEL
Date: 20191212

ACTIVE INGREDIENTS: SODIUM CHLORITE 0.21 kg/1 kg
INACTIVE INGREDIENTS: WATER

FutureGuard CD-7 Part B

DESCRIPTION

FutureGuard CD-7 Part B

WARNING

KEEP OUT OF REACH OF CHILDREN.

KEEP OUT OF DIRECT SUNLIGHT.

AVOID FREEZING.

HARMFUL IF SWALLOWED.

CAUSES SERIOUS EYE IRRITATION.

FOR FARM AND INDUSTRIAL USE ONLY.

SEE SIDE PANEL FOR FIRST AID INSTRUCTIONS

PREVENTION/ FIRST AID: Wash skin thoroughly after handling. Wear eye protection/ face protection.

FIRST AID / RESPONSE:

IF IN EYES: Rinse cautiously with water for several minutes. Remove contact lenses, if present and easy to do. Continue rinsing. If eye irritation persists: Get medical advice/ attention.

STORAGE: Store locked up.

DISPOSAL: Dispose of contents/ container to an approved waste disposal plant.

ACTIVE INGREDIENT:

Sodium Chlorite - 0.65 %

INSTRUCTIONS FOR USE

Directions for Use: FutureGuard CD-7 Part A is mixed with equal parts of FutureGuard CD-7 Part B to produce an effective teat cleaning and preparation solution. Neither product is intended for us alone.

Preparation: Follow these steps to prepare a ready to use solution:

1.Always prepare the activated solution in a well-ventilated area.

2.To prepare ready to use solution, measure equal parts of FutureGuard CD-7 Part A & FutureGuard CD-7 Part B.

3. Mix gently.

4.Let the solution stand for 15 minutes.

Application: Apply activated FutureGuard CD-7 solution prior to milking. Allow the solution to contact the teat skin surface for as long as possible prior to the drying and stimulating phase of the preparation procedure and attachment of the milking equipment. It is recommended to make up fresh FutureGuard CD-7 daily.